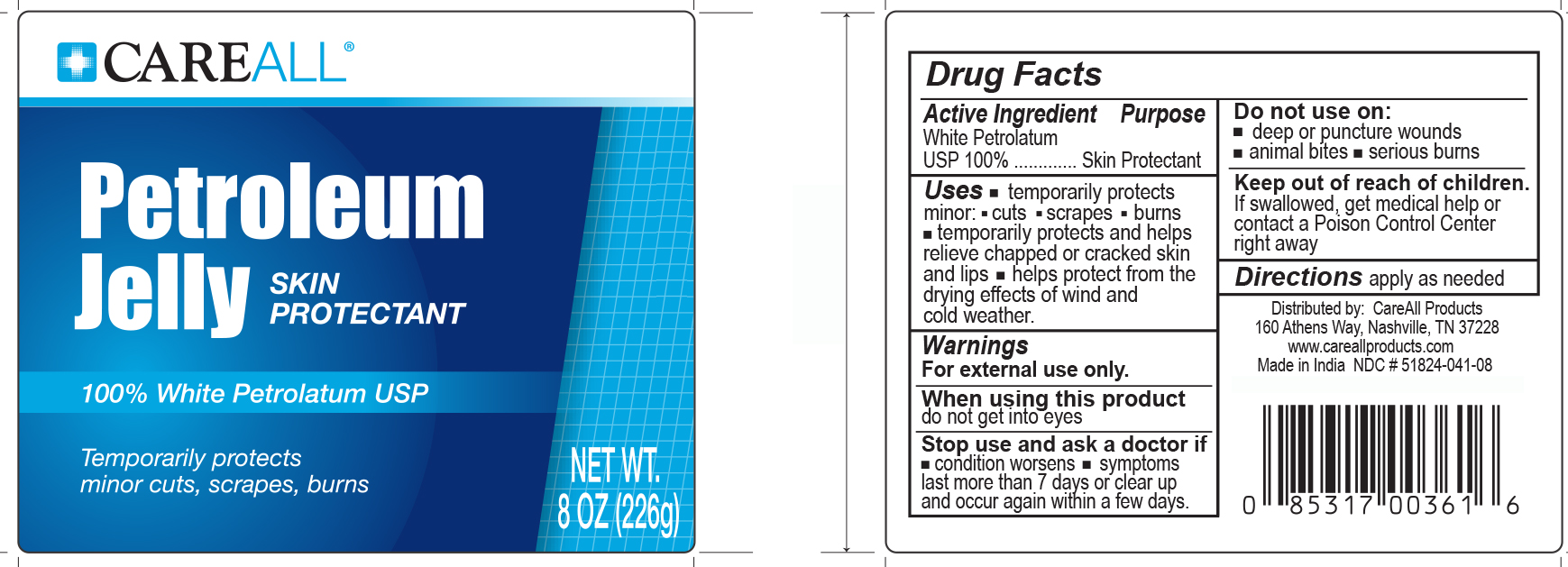 DRUG LABEL: CAREALL Petroleum
NDC: 51824-041 | Form: JELLY
Manufacturer: New World Imports, Inc
Category: otc | Type: HUMAN OTC DRUG LABEL
Date: 20251201

ACTIVE INGREDIENTS: PETROLATUM 1 g/1 g

Drug Facts

Active Ingredient

White Petrolatum USP

Purpose

Skin Protectant

Keep out of reach of children. If swallowed, get medical help or contact a Poison Control Center right away.

Indications & Uses

Temporarily protects minor cuts, scrapes and burns.

Temporarily protects and helps relieve chapped or cracked skin and lips.

Helps protect from the drying effect of wind and cold weather.

Warnings

For External use only

When using this productdo not get into eyes

Stop use and ask a doctor if

- condition worsens
- symptoms last more than 7 days or clear up and occur again within a few days

Do not use ondeep puncture wounds, animal bites, serious burns

Directions

apply as needed

inactive ingredients

none. 100% White Petrolatum